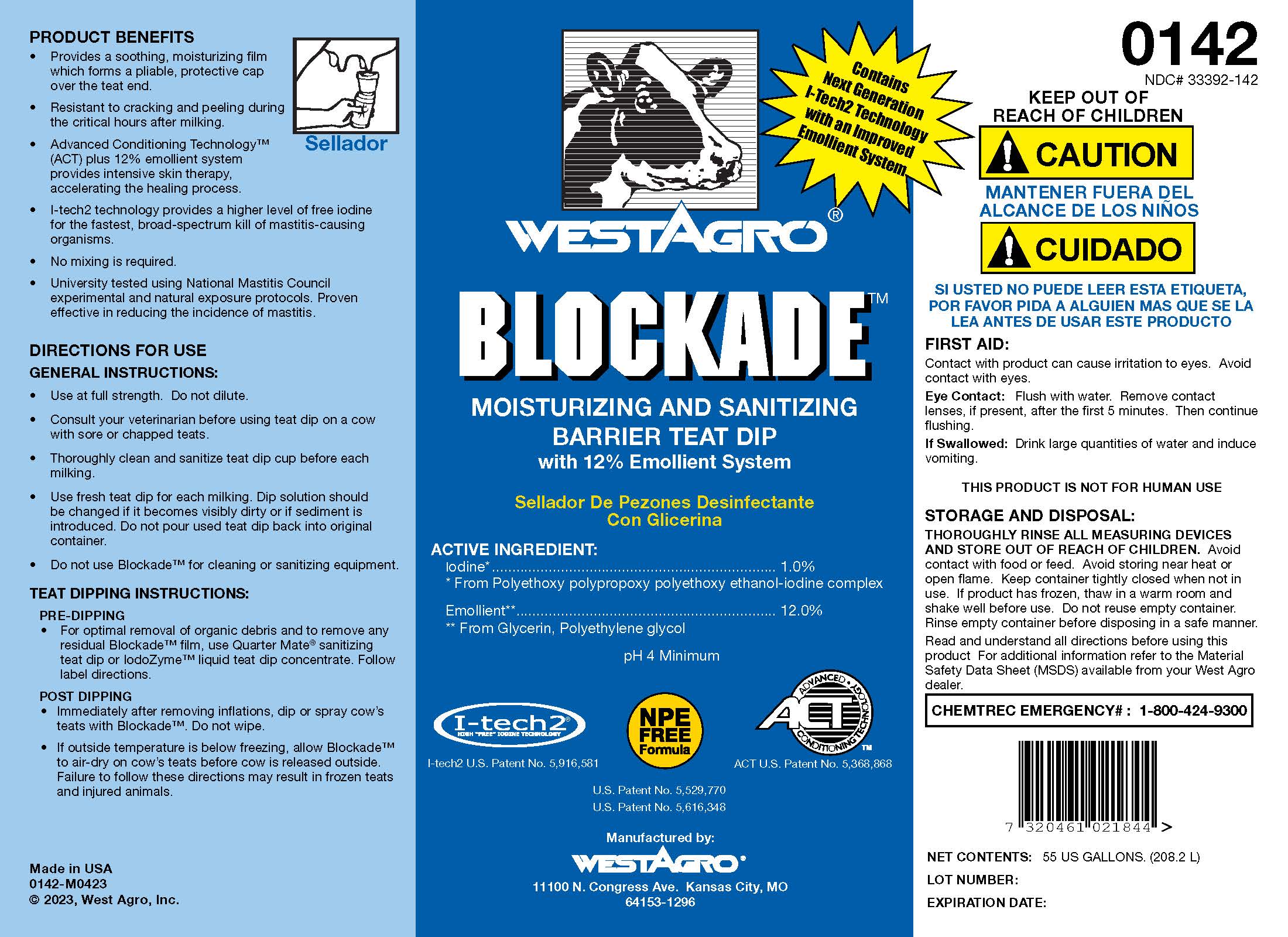 DRUG LABEL: Blockade
NDC: 33392-142 | Form: SOLUTION
Manufacturer: WestAgro, Inc.
Category: animal | Type: OTC ANIMAL DRUG LABEL
Date: 20240617

ACTIVE INGREDIENTS: IODINE 10.4 g/1 L

WESTAGRO BLOCKADE

MOISTURIZING AND SANITIZING BARRIER TEAT DIP
with 12% Emollient System

Sellador De Pezones Desinfectante Con Glicerina

ACTIVE INGREDIENT:
Iodine ............................................... 1.0%
From Polyethoxy polypropoxy polyethoxy ethanol-iodine Complex

pH 4 Minimum

I-tech2
HIGH "FREE" IODINE TECHNOLOGY

I-tech2 U.S. Patent No. 5,916,581

NPE FREE Label

ACT
ADVANCED CONDITIONING TECHNOLOGY
ACT U.S. Patent No. 5,368,868

U.S. Patent No. 5,529,770
U.S. Patent No. 5,616,348

Manufactured by:
WESTAGRO
11100 N. Congress Ave. Kansas City, MO
63153-1296

PRODUCT BENEFITS

- Provides a soothing, moisturizing film which forms a pliable, protective cap over the teat end.
- Resistant to cracking and peeling during the critical hours after milking.
- Advanced Conditioning Technology (ACT) plus 12% emollient system provides intensive skin therapy, accelerating the healing process.
- I-tech2 technology provides a higher level of free iodine for the fastest, broad-spectrum kill of mastitis-causing organisms.
- No mixing is required.
- University tested using National Mastitis Council experimental and natural exposure protocols. Proven effective in reducing the incidence of mastitis.

INDICATIONS AND USAGE

DIRECTIONS FOR USE

GENERAL INSTRUCTIONS:

- Use at full strength. Do not dilute.
- Consult your veterinarian before using teat dip on a cow with sore or chapped teats.
- Thoroughly clean and sanitize teat dip before each milking.
- Use fresh teat dip for each milking. Dip solution should be changed if it becomes visibly dirty or if sediment is introduced. Do not pour used teat dip back into original container.
- Do not use Blockade for cleaning or sanitizing equipment.

TEAT DIPPING INSTRUCTIONS:

PRE-DIPPING

- For optimal removal of organic debris and to remove any residual Blockade film, use Quarter Mate sanitizing teat dip or IodoZyme liquid teat dip concentrate. Follow label directions.

POST DIPPING

- Immediately after removing inflations, dip or spray cow's teats with Blockade. Do not wipe.

- If outside temperature is below freezing, allow Blockade to air-dry on cow's teats before cow is released outside. Failure to follow these directions may result in frozen teats and injured animals.

Made in USA
0142-I0408
Copyright, 2005, West Agro, Inc.

Contains Next Generation I-Tech2 Technology with an Improved Emollient System

0142
NDC No. 33392-142

KEEP OUT OF REACH OF CHILDREN

! CAUTION

MANTENER FUERA DEL ALCANCE DE LOS NINOS

! CUIDADO

SI USTED NO PUEDE LEER ESTA ETIQUETA, POR FAVOR PIDA A ALGUIEN MAS QUE SE LA LEA ANTES DE USAR ESTE PRODUCTO

FIRST AID:

Contact with product can cause irritation to eyes. Avoid contact with eyes.

Eye Contact: Flush with water. Remove contact lenses, if present, after the first 5 minutes. Then continue flushing.

If Swallowed: Drink large quantities of water and induce vomiting.

THIS PRODUCT IS NOT FOR HUMAN USE

STORAGE AND DISPOSAL:

THOROUGHLY RINSE ALL MEASURING DEVICES AND STORE OUT OF REACH OF CHILDREN. Avoid contact with food or feed. Avoid storing near heat or open flame. Keep container tightly closed when not in use. If product has frozen, thaw in a warm room and shake well before use. Do not reuse empty container. Rinse empty container before disposing in a safe manner.

Read and understand all directions before using this product. For additional information refer to the Material Safety Data Sheet (MSDS) available from your West Agro dealer.

CHEMTREC EMERGENCY No.
1-800-424-9300

NET CONTENTS:

LOT NO.:

EXPIRATION DATE:

PACKAGE LABEL

Add image transcription here...